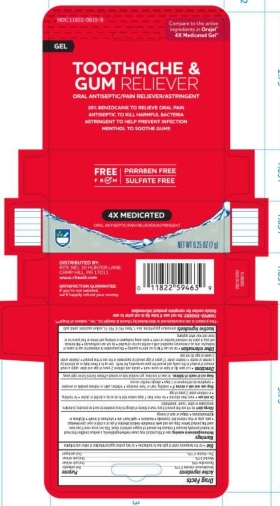 DRUG LABEL: 4X Medicated Severe Toothache and Gum Gel
NDC: 11822-0615 | Form: GEL
Manufacturer: Rite Aid
Category: otc | Type: HUMAN OTC DRUG LABEL
Date: 20251113

ACTIVE INGREDIENTS: BENZALKONIUM CHLORIDE 0.13 g/100 g; ZINC CHLORIDE 0.15 g/100 g; MENTHOL 0.5 g/100 g; BENZOCAINE 20 g/100 g
INACTIVE INGREDIENTS: AMMONIUM GLYCYRRHIZATE; POLYETHYLENE GLYCOL 3350; POLYETHYLENE GLYCOL 400; SORBIC ACID; SACCHARIN SODIUM; FD&C BLUE NO. 1; METHYL SALICYLATE

5820615 RA 4x Gel

Active Ingredients Purpose

Benzalkonium Chloride 0.13% .... Oral Antiseptic

Benzocaine 20% ......................... Oral Pain Reliever

Menthol 0.5% .............................. Oral Pain Reliever

Zinc Chloride 0.15% .................... Oral Astringent

Use

Use * for the temporary relief of pain due to toothaches * to help protect against infection of minor oral irritation

Warnings

Methemoglobinemia warning: use of this product ay cause methemoglobinemia, a serious condition that must be treated promptly because it reduces the amount of oxygen carried in teh blood. This can occur even if you have used this product before. Stop use and seek immediate medical attention if you or a child in your care develops: * pale, gray, or blue colored skin (cyanosis) * headache * rapid heart rate * shortness of breath * dizziness or lightneadedness * fatigue or lack of energy

Allergy Alert

do not use this product if you have a history of allergy to local anesthetics such as procaine, butacaine, benzocaine or other "caine" anesthetics

Do not use * more than directed * for more than 7 days unless told to do so by a dentist or doctor * for teething * in children under 2 years of age

Stop use and ask a doctor if * swelling, rash or fever develops * irritation, pain or redness persists or worsens * symptoms do not improve in 7 days * allergic reaction occurs

Keep out of reach of children. In case of overdose, get medical help or contact a Poison Control Center right away.

Directions

* cut open tip of tube to score mark * adults and children 2 years of age and older: apply a small amount of product to teh cavity and around the gum surrounding the teeth. Use up to 4 times daily or as directed by a dentist or doctor * children under 12 years of age should be supervised in the use of this product * children under 2 years of age: do not use

Other Information

Other information * do not use if tip is cut prior to ening * this preparation is intended for use in cases of toothache, only as a temporary expedient until a dentist can be consulted * do not use ontinuously * this formula will stay in place for extended duration of reilef * avoid using toothpaste or drinking soft drinks or fruit juices for at least one hour after applying

INACTIVE INGREDIENT

ammonium glycyrrhizate, blue 1, flavor, PEG-8, PEG-75, sodium saccharin, sorbic acid